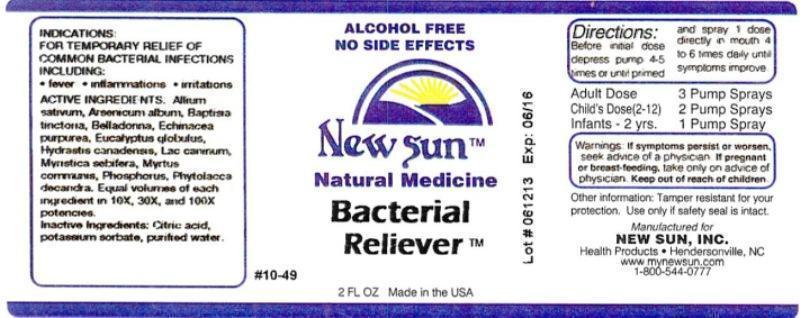 DRUG LABEL: Bacterial Reliever
NDC: 66579-0023 | Form: LIQUID
Manufacturer: New Sun Inc.
Category: homeopathic | Type: HUMAN OTC DRUG LABEL
Date: 20140918

ACTIVE INGREDIENTS: GARLIC 10 [hp_X]/59 mL; ARSENIC TRIOXIDE 10 [hp_X]/59 mL; BAPTISIA TINCTORIA ROOT 10 [hp_X]/59 mL; ATROPA BELLADONNA 10 [hp_X]/59 mL; ECHINACEA PURPUREA 10 [hp_X]/59 mL; EUCALYPTUS GLOBULUS LEAF 10 [hp_X]/59 mL; GOLDENSEAL 10 [hp_X]/59 mL; CANIS LUPUS FAMILIARIS MILK 10 [hp_X]/59 mL; MYRTUS COMMUNIS TOP 10 [hp_X]/59 mL; VIROLA SEBIFERA RESIN 10 [hp_X]/59 mL; PHOSPHORUS 10 [hp_X]/59 mL; PHYTOLACCA AMERICANA ROOT 10 [hp_X]/59 mL
INACTIVE INGREDIENTS: CITRIC ACID MONOHYDRATE; POTASSIUM SORBATE; WATER

Bacterial Reliever

DOSAGE AND ADMINISTRATION

Directions: Before initial dose depress pump 4-5 times or until primed and spray 1 dose directly in mouth 4 to 6 times daily until symptoms improve.

Adult Dose: 3 Pump Sprays

Child's Dose (2-12): 2 Pump Sprays

Infants - 2 yrs: 1 Pump Spray

WARNINGS

Warnings: If symptoms persist or worsen, seek advice of a physician. If pregnant or breast-feeding, take only on advice of physician.

Keep out of reach of children.

Other information: Tamper resistant for your protection. Use only if safety seal is intact.

PURPOSE

Indications: For temporary relief of common bacterial infections including: • fever • inflammations • irritations

ACTIVE INGREDIENT

Active Ingredients: Allium sativum, Arsenicum album, Baptisia tinctoria, Belladonna, Echinacea purpurea, Eucalyptus globulus, Hydrastis canadensis, Lac caninum, Myristica sebifera, Myrtus communis, Phosphorus, Phytolacca decandra. Equal volumes of each ingredient in 10X, 30X, 100X potencies.

Inactive Ingredients: Citric acid, potassium sorbate, purified water.

INDICATIONS AND USAGE

Indications: For temporary relief of common bacterial infections including:

- fever
- inflammations
- irritations